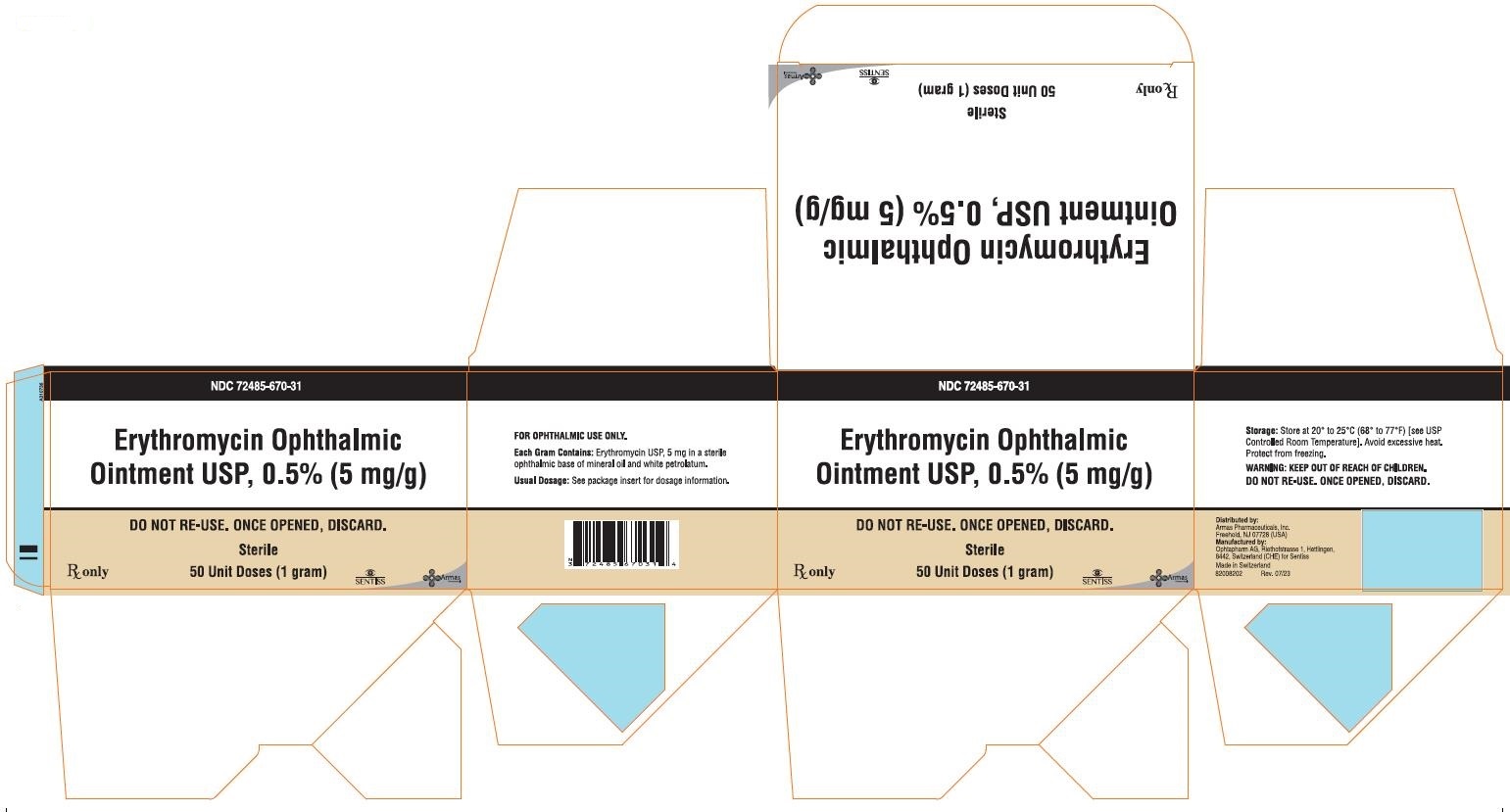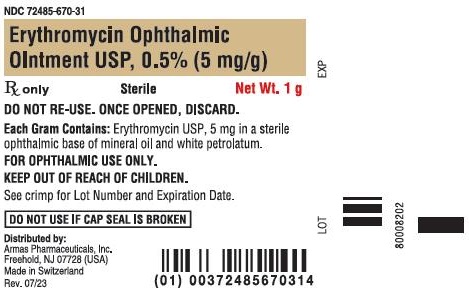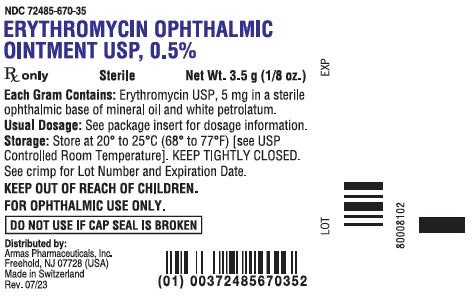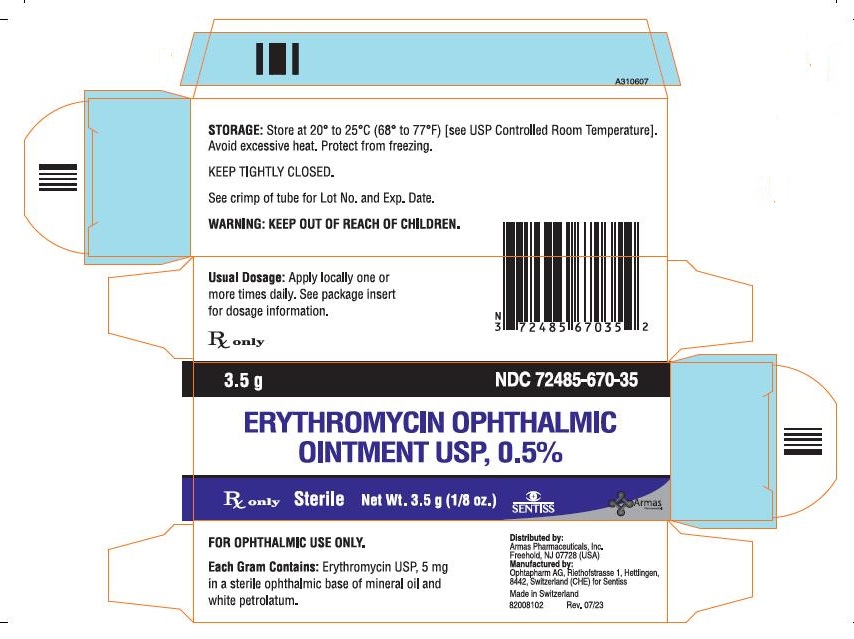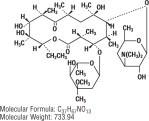 DRUG LABEL: Erythromycin
NDC: 67296-2128 | Form: OINTMENT
Manufacturer: Redpharm Drug
Category: prescription | Type: HUMAN PRESCRIPTION DRUG LABEL
Date: 20251223

ACTIVE INGREDIENTS: ERYTHROMYCIN 5 mg/1 g
INACTIVE INGREDIENTS: MINERAL OIL; PETROLATUM

Erythromycin Ophthalmic Ointment USP, 0.5%

Sterile

Rx only

DESCRIPTION:

Erythromycin Ophthalmic Ointment belongs to the macrolide group of antibiotics. It is basic and readily forms a salt when combined with an acid. The base, as crystals or powder, is slightly soluble in water, moderately soluble in ether, and readily soluble in alcohol or chloroform. Erythromycin ((3R*, 4S*, 5S*, 6R*, 7R*, 9R*, 11R*, 12R*, 13S*, 14R*)-4-[(2,6-dideoxy-3-C-methyl-3- O-methyl-α-L- ribo-hexopyranosyl)-oxy]-14-ethyl-7,12,13-trihydroxy-3,5,7,9,11,13-hexamethyl-6-[[3,4,6-trideoxy-3-(dimethyl-amino)-β-D- xylo-hexopyranosyl]oxy]oxacyclotetradecane-2,10-dione)) is an antibiotic produced from a strain of Streptomyces erythraeus.

It has the following structural formula:

Each gram contains Erythromycin USP 5 mg in a sterile ophthalmic base of mineral oil and white petrolatum.

CLINICAL PHARMACOLOGY:

MICROBIOLOGY

Microbiology:Erythromycin inhibits protein synthesis without affecting nucleic acid synthesis. Erythromycin is usually active against the following organisms in vitroand in clinical infections:

Streptococcus pyogenes(group A β-hemolytic)

Alpha-hemolytic streptococci (viridans group)

Staphylococcus aureus, including penicillinase-producing strains (methicillin-resistant staphylococci are uniformly resistant to erythromycin)

Streptococcus pneumoniae

Mycoplasma pneumoniae(Eaton Agent, PPLO)

Haemophilus influenzae(not all strains of this organism are susceptible at the erythromycin concentrations ordinarily achieved)

Treponema pallidum

Corynebacterium diphtheriae

Neisseria gonorrhoeae

Chlamydia trachomatis

INDICATIONS AND USAGE:

For the treatment of superficial ocular infections involving the conjunctiva and/or cornea caused by organisms susceptible to erythromycin.

For prophylaxis of ophthalmia neonatorum due to N. gonorrhoeaeor C. trachomatis.

The effectiveness of erythromycin in the prevention of ophthalmia caused by penicillinase-producing N.gonorrhoeaeis not established.

For infants born to mothers with clinically apparent gonorrhea, intravenous or intramuscular injections of aqueous crystalline penicillin G should be given; a single dose of 50,000 units for term infants or 20,000 units for infants of low birth weight. Topical prophylaxis alone is inadequate for these infants.

CONTRAINDICATIONS:

This drug is contraindicated in patients with a history of hypersensitivity to erythromycin.

PRECAUTIONS:

GENERAL PRECAUTIONS

General:The use of antimicrobial agents may be associated with the overgrowth of nonsusceptible organisms including fungi; in such a case, antibiotic administration should be stopped and appropriate measures taken.

PATIENT COUNSELING INFORMATION

Information for Patients:Avoid contaminating the applicator tip with material from the eye, fingers, or other source.

CARCINOGENESIS AND MUTAGENESIS AND IMPAIRMENT OF FERTILITY

Carcinogenesis, Mutagenesis, Impairment of Fertility:Two year oral studies conducted in rats with erythromycin did not provide evidence of tumorigenicity. Mutagenicity studies have not been conducted. No evidence of impaired fertility that appeared related to erythromycin was reported in animal studies.

PREGNANCY

Pregnancy:Teratogenic Effects: Pregnancy Category B. Reproduction studies have been performed in rats, mice, and rabbits using erythromycin and its various salts and esters, at doses that were several multiples of the usual human dose. No evidence of harm to the fetus that appeared related to erythromycin was reported in these studies. There are, however, no adequate and well controlled studies in pregnant women. Because animal reproductive studies are not always predictive of human response, the erythromycins should be used during pregnancy only if clearly needed.

NURSING MOTHERS

Nursing Mothers:Caution should be exercised when erythromycin is administered to a nursing woman.

PEDIATRIC USE

Pediatric Use -See INDICATIONS AND USAGEand DOSAGE AND ADMINISTRATION.

GERIATRIC USE

Geriatric Use:No overall differences in safety or effectiveness have been observed between elderly and younger patients.

ADVERSE REACTIONS:

The most frequently reported adverse reactions are minor ocular irritations, redness, and hypersensitivity reactions.

DOSAGE AND ADMINISTRATION:

In the treatment of superficial ocular infections, a ribbon approximately 1 cm in length of Erythromycin Opthalmic Ointment should be applied directly to the infected structure up to 6 times daily, depending on the severity of the infection.

For prophylaxis of neonatal gonococcal or chlamydial conjunctivitis, a ribbon of ointment approximately 1 cm in length should be instilled into each lower conjunctival sac. The ointment should not be flushed from the eye following instillation. A new tube should be used for each infant.

HOW SUPPLIED:

Sterile Erythromycin Ophthalmic Ointment USP, 0.5% is available as follows:

3.5 g (1/8 oz) sterile tamper-resistant tube (NDC 72485-670-35)

Carton of fifty (50) Unit Dose 1 g tube (NDC 72485-670-31)

STORAGE AND HANDLING

STORAGE:Store at 20° to 25°C (68° to 77°F) [see USP Controlled Room Temperature].

Avoid excessive heat.

Protect from freezing.

Distributed by:

Armas Pahrmaceuticals, Inc.

Freehold, NJ 07728 (USA)

Manufactured by:

Ophtapharm AG, Riethofstrasse 1, Hellingen,

8442, Switzerland (CHE) for Sentiss

Made in Switzerland

83008101 Rev. 07/23

Principal Display Panel Text for Container Label

NDC 72485-670-35

ERYTHROMYCIN OPHTHALMIC

OINTMENT USP, 0.5%

Rx only Sterile Net Wt. 3.5 g (1/8 oz.)

NDC 72485-670-31

ERYTHROMYCIN OPHTHALMIC

OINTMENT USP, 0.5%

Rx only Sterile Net Wt. 1 g

Principal Display Panel Text for Carton Label

3.5 g NDC 72485-670-35

ERYTHROMYCIN OPHTHALMIC

OINTMENT USP, 0.5%

Rx only Sterile Net Wt 3.5 g (1/8 oz.)

1 g NDC 72485-670-31

ERYTHROMYCIN OPHTHALMIC

OINTMENT USP, 0.5%

Rx only Sterile Net Wt 1 g